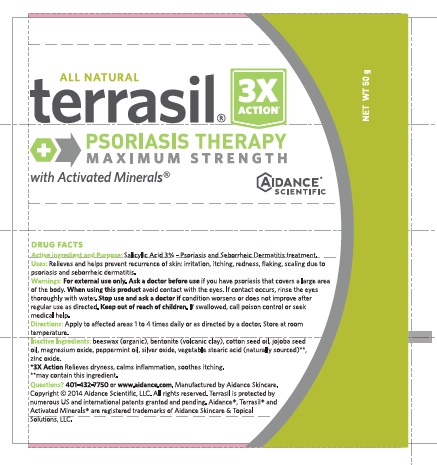 DRUG LABEL: Terrasil Psoriasis Therapy
NDC: 24909-134 | Form: OINTMENT
Manufacturer: Aidance Skincare & Topical Solutions, LLC
Category: otc | Type: HUMAN OTC DRUG LABEL
Date: 20181229

ACTIVE INGREDIENTS: SALICYLIC ACID 3 g/100 g
INACTIVE INGREDIENTS: BENTONITE; COTTONSEED OIL; JOJOBA OIL; MAGNESIUM OXIDE; PEPPERMINT OIL; SILVER OXIDE; STEARIC ACID; WHITE WAX; ZINC OXIDE

Drug Facts

Active Ingredients

Salicylic Acid 3%

Purpose

Psoriasis and Seborrheic Dermatitis Treatment

Uses

Relieves and helps prevent recurrence of skin: - irritation, - itching, - redness, - flaking, - scaling due to psoriasis and seborrheic dermatitis

Warnings

For external use only.

Directions

Apply to affected areas one to four times daily or as directed by a doctor. Store at room temperature.

Inactive Ingredients

beeswax (organic), bentonite (volcanic clay), cotton seed oil, jojoba seed oil, magnesium oxide, peppermint oil, silver oxide, stearic acid (naturally sourced), zinc oxide.

PRINCIPAL DISPLAY PANEL - 50g Tube

All Natural
terrasil®
PSORIASIS THERAPY
MAXIMUM STRENGTH
with Activated Minerals®